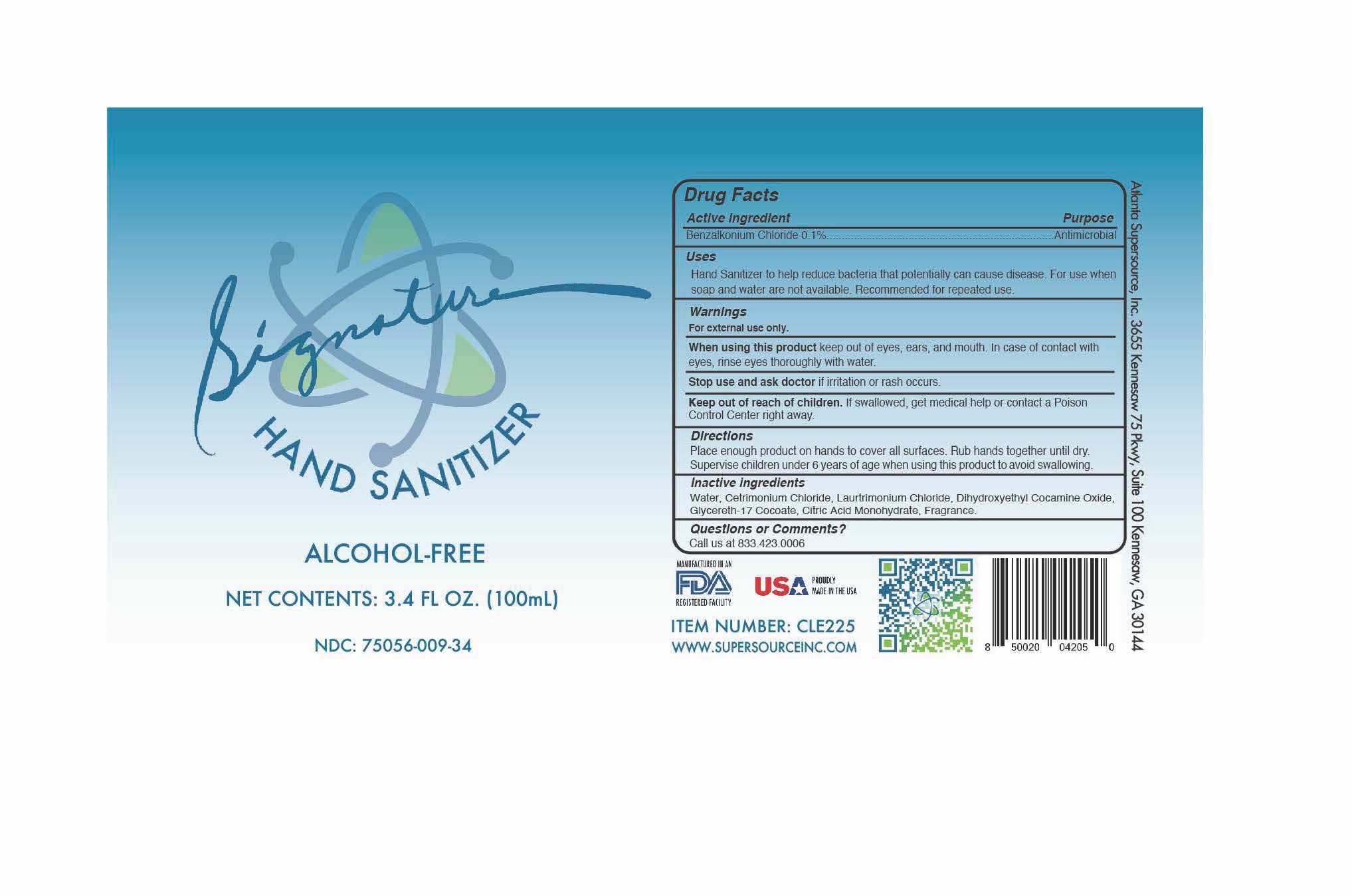 DRUG LABEL: Hand Sanitizer
NDC: 75056-009 | Form: SPRAY
Manufacturer: Atlanta Supersource, Inc.
Category: otc | Type: HUMAN OTC DRUG LABEL
Date: 20221227

ACTIVE INGREDIENTS: BENZALKONIUM CHLORIDE 0.1 g/100 g
INACTIVE INGREDIENTS: WATER 99.8703 g/100 g; DIHYDROXYETHYL COCAMINE OXIDE 0.0099 g/100 g; LAURTRIMONIUM CHLORIDE 0.0099 g/100 g; CETRIMONIUM CHLORIDE 0.0099 g/100 g

Supersource Hand Sanitizer Alcohol Free

Supersource Hand Sanitizer

Alcohol Free

Net Contents:3.4 FL OZ. (100mL)

NDC: 75056-009-34

Item No: CLE225

Atlanta Supersource, Inc.

3655 Kennesaw 75 Parkway, Suite 100

Kennesaw, GA 30144

Active Ingredient

Benzalkonium Chloride 0.1%

Purpose

Antimicrobial

Uses

Hand Sanitizer to help reduce bacteria that can potentially cause disease. For use when soap and water are not available. Recommended for repeated use.

Warnings

For external use only.

When using this product

keep out of eyes, ears and mouth. In case of contact with eyes, rinse eyes thoroughly with water.

Stop use and ask doctor

if irritation or rash occurs.

Keep out of reach of children

If swallowed, get medical help or contact a Poison Control Center right away.

Directions

Place enough product on hands to cover all surfaces. Rub hands together until dry. Supervise children under 6 years of age when using this product to avoid swallowing.

Inactive Ingredients

Water, Cetrimonium Chloride, Laurtrimonium Chloride, Dihydroxyethyl Cocamine Oxide, Glycereth-17 Cocoate, Citric Acid Monohydrate, Fragrance.

Questions or Comments?

Call us at 833.423.0006

Signature Hand Sanitizer Alcohol Free

NET CONTENTS: 3.4 OZ (100mL)